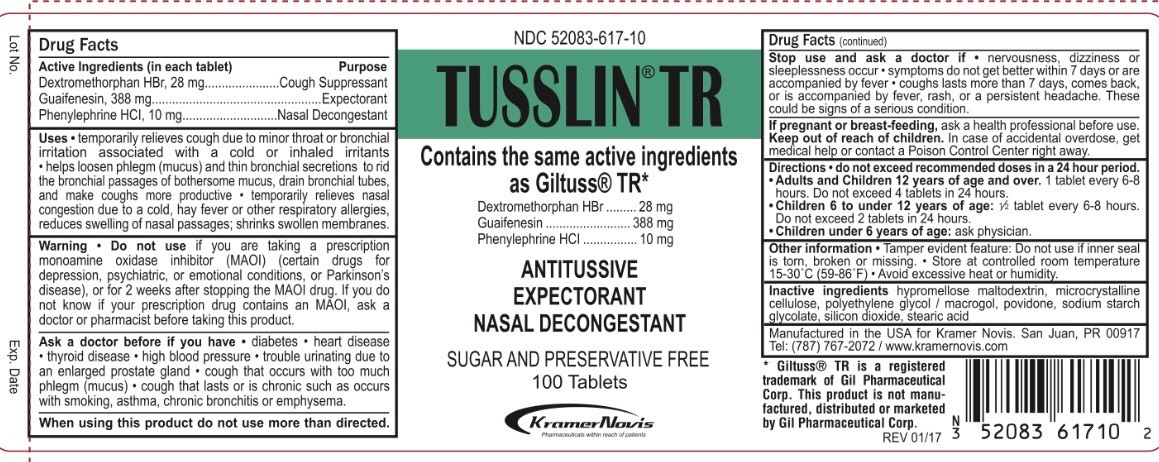 DRUG LABEL: Tusslin TR
NDC: 52083-617 | Form: TABLET
Manufacturer: KRAMER NOVIS
Category: otc | Type: HUMAN OTC DRUG LABEL
Date: 20171226

ACTIVE INGREDIENTS: DEXTROMETHORPHAN HYDROBROMIDE 28 1/1 1; GUAIFENESIN 388 1/1 1; PHENYLEPHRINE HYDROCHLORIDE 10 1/1 1
INACTIVE INGREDIENTS: HYPROMELLOSES; MALTODEXTRIN; CELLULOSE, MICROCRYSTALLINE; POLYETHYLENE GLYCOL 3350; POVIDONE; SODIUM STARCH GLYCOLATE TYPE A CORN; STEARIC ACID

DRUG FACTS

ACTIVE INGREDIENT

Active Ingredients(in each tablet): Guaifenesin 388 mg, dextromethorphan hydrobromide 28 mg, phenylephrine hydrochloride 10 mg

PURPOSE

Cough Suppressant, Expectorant, Nasal Decongestant

INDICATIONS AND USAGE

Uses • temporarily relieves cough due to minor throat or bronchial irritation associated with a cold or inhaled irritants • helps loosen phlegm (mucus) and thin bronchial secretions to rid the bronchial passages of bothersome mucus, drain bronchial tubes, and make coughs more productive • temporarily relieves nasal congestion due to a cold, hay fever or other respiratory allergies, reduces swelling of nasal passages; shrinks swollen membranes

WARNINGS

Warning • Do not use if you are taking a prescription monoamine oxidase inhibitor (MAOI) (certain drugs for depression, psychiatric, or emotional conditions, or Parkinson’s disease), or for 2 weeks after stopping the MAOI drug. If you do not know if your prescription drug contains an MAOI, ask a doctor or pharmacist before taking this product.

Ask a doctor before if you have • diabetes • heart disease • Thyroid disease • high blood pressure • trouble urinating due to an enlarged prostate gland • cough that occurs with too much phlegm (mucus) • cough that lasts or is chronic such as occurs with smoking, asthma, chronic bronchitis or emphysema.

When using this product do not use more than directed.

Stop use and ask a doctor if • nervousness, dizziness or sleeplessness occur • symptoms do not get better within 7 days or are accompanied by fever • coughs lasts more than 7 days, comes back, or is accompanied by fever, rash, or a persistent headache. These could be signs of a serious condition.

Keep out of reach of children. In case of accidental overdose, get medical help or contact a Poison Control Center right away.

PREGNANCY OR BREAST FEEDING

If pregnant or breast-feeding, ask a health professional before use.

Inactive ingredients

Hypromellose Maltodextrin, Microcrystalline Cellulose, Polyethylene Glycol / Macrogol, Povidone, Sodium Starch Glycolate, Stearic Acid

DOSAGE AND ADMINISTRATION

Directions • do not exceed recommended doses in a 24 hour period.

• Adults and Children 12 years of age and over. 1 tablet every 6-8 hours. Do not exceed 4 tablets in 24 hours.

• Children 6 to under 12 years of age: 1⁄2 tablet every 6-8 hours. Do not exceed 2 tablets in 24 hours.

• Children under 6 years of age: ask physician.